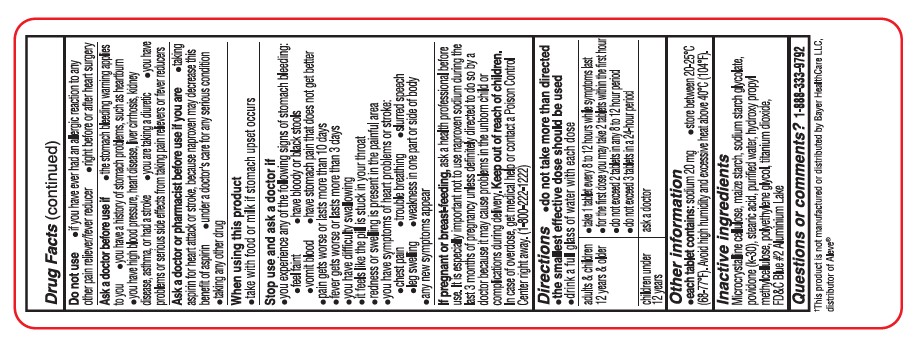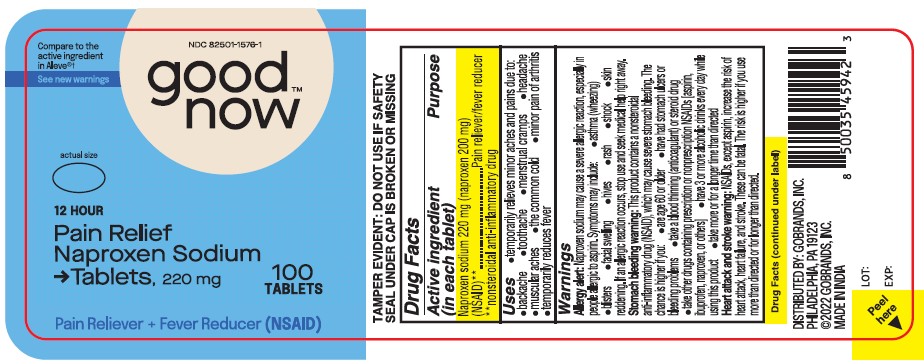 DRUG LABEL: Pain Relief
NDC: 82501-1576 | Form: TABLET, FILM COATED
Manufacturer: Gobrands, Inc
Category: otc | Type: HUMAN OTC DRUG LABEL
Date: 20241220

ACTIVE INGREDIENTS: NAPROXEN SODIUM 220 mg/1 1
INACTIVE INGREDIENTS: MICROCRYSTALLINE CELLULOSE; STARCH, POTATO; SODIUM STARCH GLYCOLATE TYPE A; POVIDONE K30; STEARIC ACID; METHYLCELLULOSE, UNSPECIFIED; POLYETHYLENE GLYCOL, UNSPECIFIED; TITANIUM DIOXIDE; FD&C BLUE NO. 1 ALUMINUM LAKE

Pain Relief
Naproxen Sodium

Active Ingredient (in each tablet)

Naproxen Sodium 220 mg**

**nonsteroidal anti-inflammatory drug

Purpose

Pain reliever/fever reducer

Uses

- temporarily relieves minor aches and pains due to:
- backache n headache n menstrual cramps
- minor pain of arthritis n muscular aches
- the common cold n toothache
- temporarily reduces fever

Warnings

Allergy alert: Naproxen sodium may cause a severe allergic reaction, especially in people allergic to aspirin.
Symptoms may include:

- asthma (wheezing)
- blisters
- facial swelling
- hives
- rash
- shock
- skin reddening

If an allergic reaction occurs, stop use and seek medical help right away.

Stomach bleeding warning: This product contains a nonsteroidal anti-inflammatory drug (NSAID), which may cause severe stomach bleeding. The chance is higher if you:

- are age 60 or older
- have had stomach ulcers or bleeding problems
- take a blood thinning (anticoagulant) or steroid drug
- take other drugs containing prescription or nonprescription NSAIDs [aspirin, ibuprofen, naproxen, or others]
- have 3 or more alcoholic drinks every day while using this product
- take more or for a longer time than directed

Heart attack and stroke warning: NSAIDs, except aspirin increase the risk of heart attack, heart failure, and stroke. These can be fatal. The risk is higher if you use more than directed or for longer than directed.

Do not use:

- if you have ever had an allergic reaction to any other pain reliever/fever reducer
- right before or after heart surgery

Ask a doctor before use if you

- the stomach bleeding warning applies to you
- you have a history of stomach problems, such as heartburn
- you have high blood pressure, heart disease, liver cirrhosis, kidney disease, asthma, or had a stroke
- you are taking a diuretic
- you have problems or serious side effects from taking pain relievers or fever reducers

Ask a doctor or pharmacist before use if you are if you are

- under a doctor's care for any serious condition
- taking any other drug
- taking aspirin for heart attack or stroke, because naproxen may decrease this benefit of aspirin

When using this product

- take with food or milk if stomach upset occurs

Stop use and ask a doctor if

- you experience any of the following signs of stomach bleeding: n feel faint n vomit blood
- have bloody or black stools
- have stomach pain that does not get better
- you have symptoms of heart problems or stroke:
- chest pain
- trouble breathing
- weakness in one part or side of body
- slurred speech n leg swelling
- pain gets worse or lasts more than 10 days
- fever gets worse or lasts more than 3 days
- you have difficulty swallowing
- it feels like the pill is stuck in your throat
- redness or swelling is present in the painful area
- any new symptoms appear

PREGNANCY OR BREAST FEEDING

If pregnant or breast-feeding, ask a health professional before use. It is especially important not to use naproxen sodium during the last 3 months of pregnancy unless definitely directed to do so by a doctor because it may cause problems in the unborn child or complications during delivery.

Keep out of reach of children. In case of overdose, get medical help or contact a Poison Control Center right away (1-800-222-1222).

Directions

- do not take more than directed
- the smallest effective dose should be used
- drink a full glass of water with each dose

adults and children 12 years and older: | - take 1 tablet every 8 to 12 hours while symptoms last - for the first dose you may take 2 tablets within the first hour - do not exceed 2 tablets in any 8 to 12 hour period - do not exceed 3 tablets in a 24-hour period
children under 12 years: | - ask a doctor

Other information

- each tablet contains: sodium 20 mg
- store between 20˚-25˚C (68˚-77˚F). Avoid high humidity and excessive heat above 40˚C (104˚F)

Inactive ingredients

Microcrystalline cellulose, Starch, Sodium starch glycolate, povidone (K-30), stearic acid, purified water, hydroxy propyl methylcellulose, polyethylene glycol, titanium dioxide, FD&C Blue #2 aluminum lake

Questions or comments?

1-888-333-9792

PRINCIPAL DISPLAY PANEL

Compare to the active ingredient in Aleve

NDC 82501-1576-1

Good now

12 HOUR
Pain Relief
Naproxen Sodium Tablets, 220 mg

100 TABLETS

Pain Reliever + Fever Reducer (NSAID)